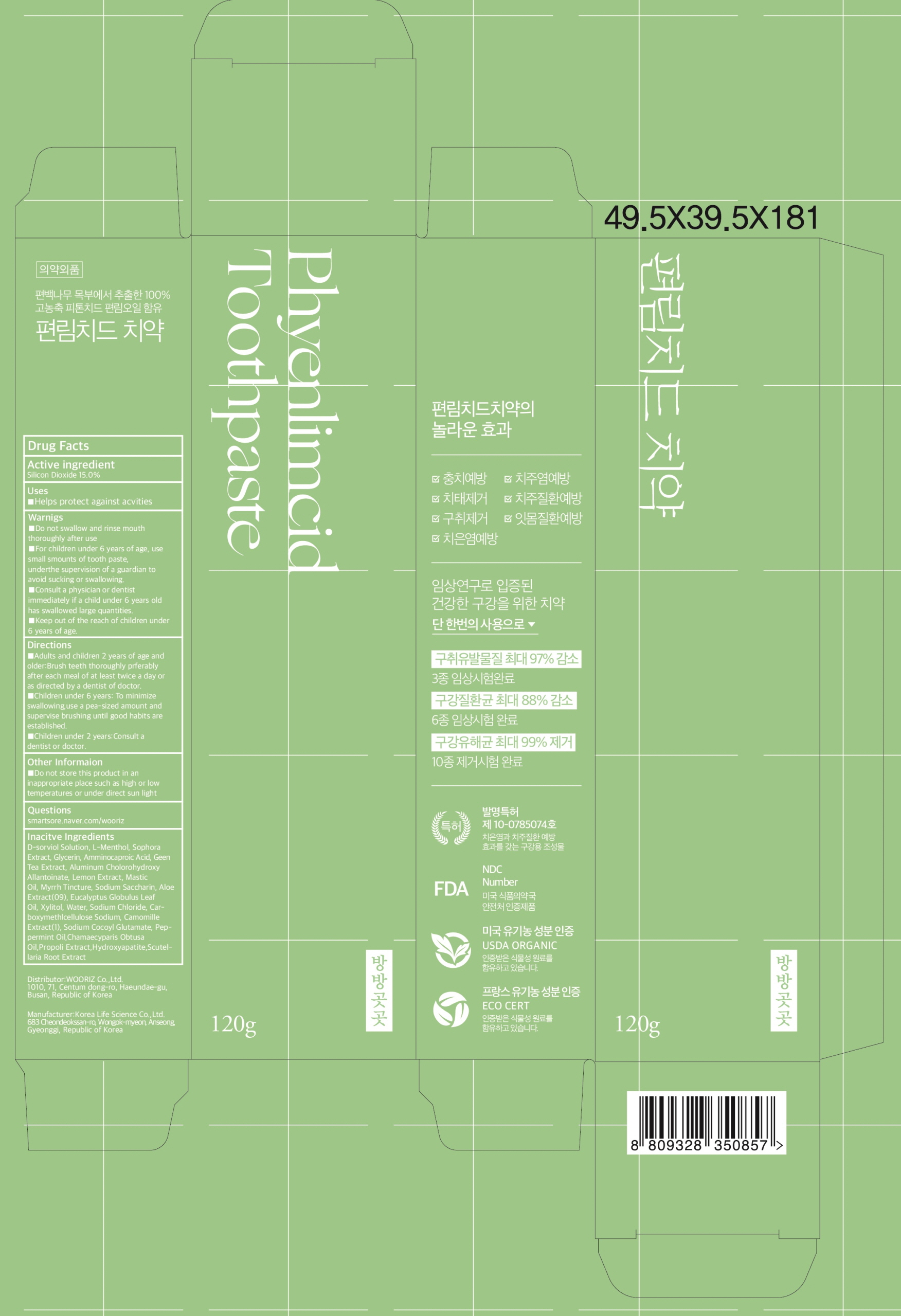 DRUG LABEL: PHYENLIMCIDE TOOTHPASTE
NDC: 82336-020 | Form: PASTE, DENTIFRICE
Manufacturer: WOORIZ Co.,Ltd.
Category: otc | Type: HUMAN OTC DRUG LABEL
Date: 20230410

ACTIVE INGREDIENTS: Silicon Dioxide 15.0 g/100 g
INACTIVE INGREDIENTS: SORBITOL; LEVOMENTHOL

ACTIVE INGREDIENT

Silicon Dioxide 15.0%

PURPOSE

Anticavity

Uses

■ Helps protect against cavities

WARNINGS

■ Do not swallow and rinse mouth thoroughly after use
■ For children under 6 years of age, use small amounts of toothpaste.
under the supervision of a guardian to avoid sucking or swallowing.
■ Consult a physician or dentist immediately if a child under 6 years old has
swallowed large quantities.
■ Keep out of the reach of children under 6 years of age.

KEEP OUT OF REACH OF CHILDREN

■ Keep out of the reach of children under 6 years of age.

Directions

■ Adults and children 2 years of age and older: Brush teeth thoroughly preferably after each meal or at least twice a day or as directed by a dentist or doctor.
■ Children under 6 years: To minimize swallowing, use a pea-sized amount and supervise brushing until good habits are established.
■ Children under 2 years: Consult a dentist or doctor.

Other Information

■Do not store this product in an inappropriate place such as high or low temperatures or under direct sun light

Questions

smartstore.naver.com/wooriz

INACTIVE INGREDIENTS

D-sorbitol Solution,L-Menthol,Sophora Extract,Glycerin,Aminocaproic Acid,Geen Tea Extract,Aluminum Chlorohydroxy Allantoinate,Lemon Extract,Mastic Oil,Myrrh Tincture,Sodium Saccharin,Aloe Extract(09),Eucalyptus Globulus Leaf Oil,Xylitol,Water,Sodium Chloride,Carboxymethylcellulose Sodium,Camomille Extract(1),Sodium Cocoyl Glutamate,Peppermint Oil,Chamaecyparis Obtusa Oil,Propolis Extract,Hydroxyapatite,Scutellaria Root Extract